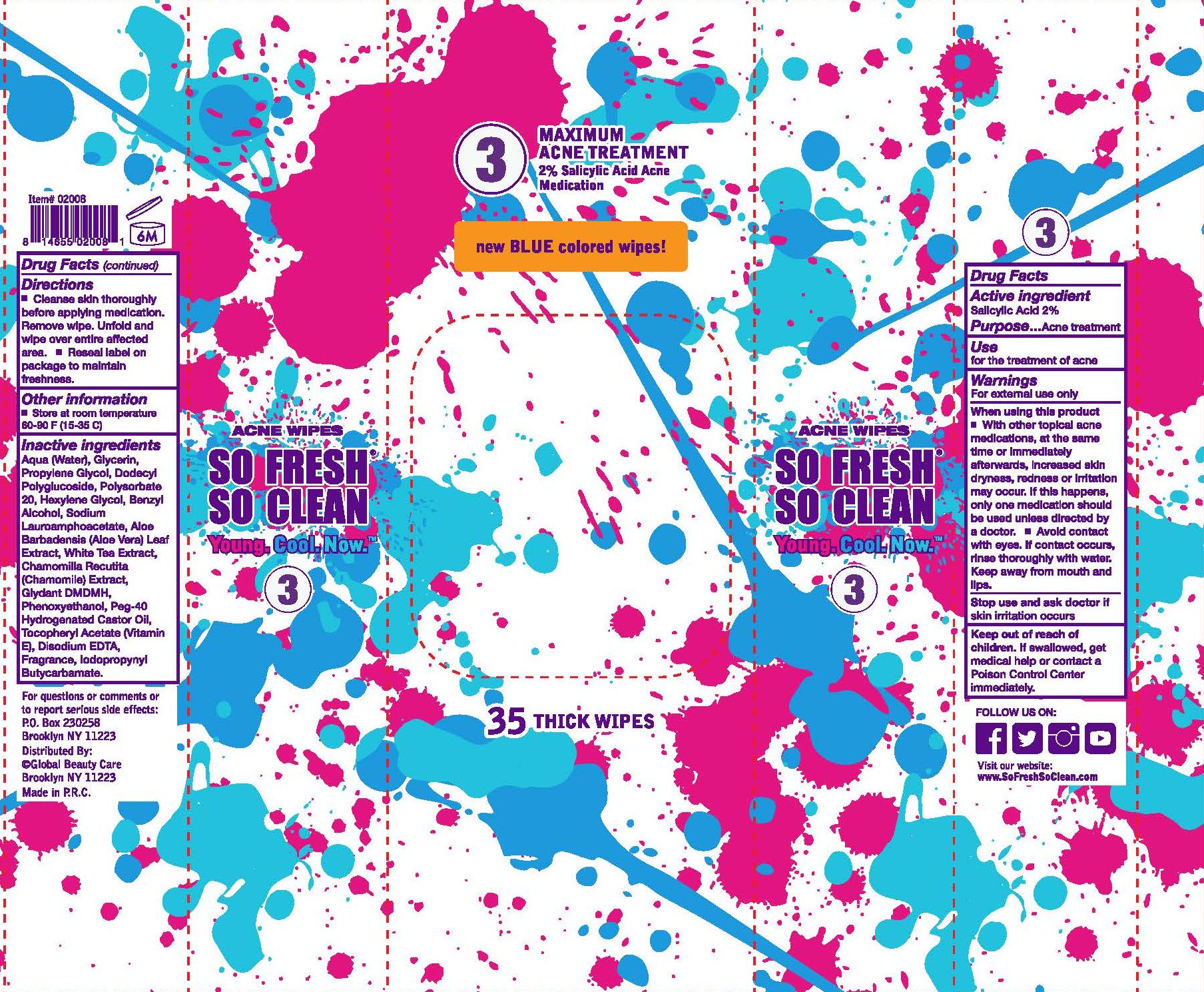 DRUG LABEL: So Fresh So Clean Maximum Acne Treatment
NDC: 69722-735 | Form: CLOTH
Manufacturer: Global Beauty Care, Inc.
Category: otc | Type: HUMAN OTC DRUG LABEL
Date: 20150625

ACTIVE INGREDIENTS: SALICYLIC ACID 2 g/100 g
INACTIVE INGREDIENTS: IODOPROPYNYL BUTYLCARBAMATE; DMDM HYDANTOIN; PHENOXYETHANOL; ALPHA-TOCOPHEROL ACETATE; WATER; GLYCERIN; PROPYLENE GLYCOL; POLYSORBATE 20; HEXYLENE GLYCOL; BENZYL ALCOHOL; SODIUM LAUROAMPHOACETATE; GREEN TEA LEAF; POLYOXYL 40 HYDROGENATED CASTOR OIL; EDETATE DISODIUM; ALOE VERA LEAF; MATRICARIA RECUTITA

SO FRESH SO CLEAN MAXIMUM ACNE TREATMENT

SO FRESH SO CLEAN MAXIMUM ACNE TREATMENT 2% Salicylic Acid Acne Medication

35 THICK WIPES

Active ingredient

Salicylic Acid 2%

Purpose

Acne treatment

Use

for the treatment of acne

Warnings

For external use only

When using this product

- With other topical acne medications, at the same time or immediately afterwards, increased skin dryness, redness or irritation may occur. If this happens, only one medicationshould be used unless directed by a doctor.
- Avoid contact with eyes. If contact occurs, rinse thoroughly with water. Keep away from mouth and lips.

Stop use and ask doctor if

skin irritation occurs

Keep out of reach of children.

If swallowed, get medical help or contact a Poison Control Center immediately.

Directions

- Cleanse skin thoroughly before applying medication. Remove wipe. Unfold and wipe over entire affected area.
- Reseal label on package to maintain freshness.

Other information

- Store at room temperature 60-90F (15-35 C)

Inactive ingredients

Aqua (Water), Glycerin, Propylene Glycol, Dodecyl Polyglucoside, Polysorbate 20, Hexylene Glycol, Benzyl Alcohol,Sodium Lauroamphoacetate, Aloe Barbadensis (Aloe Vera) Leaf Extract, White TEa Extract, Chamomilla Recutita (Chamomile) Extreact, Glydant DMDMH, Phenoxyethanol, Peg-40 Hydrogenated Castor Oil, Tocopheryl Acetate (Vitamin E)., Disodium EDTA, Fragrance, Iodopropynyl Butycarbamate.

QUESTIONS

For questions or comments or to report serious side effects:

P.O. Box 230258

Brooklyn, NY 11223